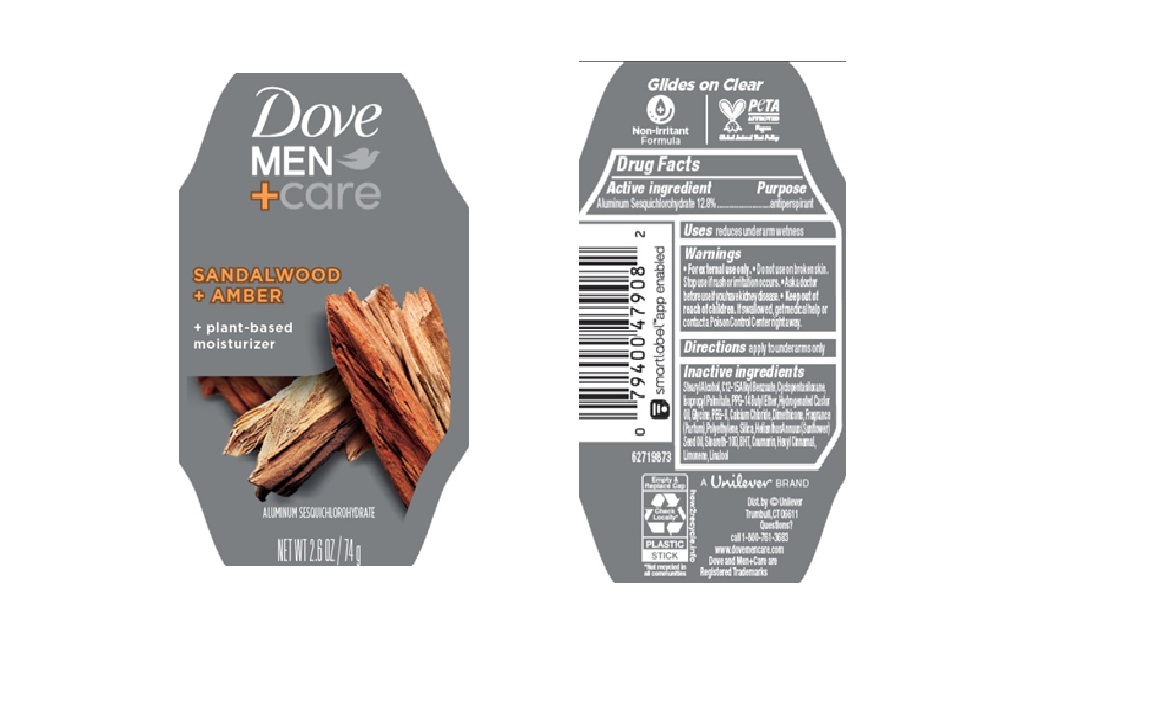 DRUG LABEL: Dove
NDC: 64942-2359 | Form: STICK
Manufacturer: Conopco d/b/a/ Unilever
Category: otc | Type: HUMAN OTC DRUG LABEL
Date: 20250331

ACTIVE INGREDIENTS: ALUMINUM SESQUICHLOROHYDRATE 12.8 g/100 g
INACTIVE INGREDIENTS: ISOPROPYL PALMITATE; PEG-8; POLYETHYLENE; HELIANTHUS ANNUUS (SUNFLOWER) SEED OIL; COUMARIN; HYDROGENATED CASTOR OIL; HEXYL CINNAMAL; LIMONENE, (+)-; CYCLOPENTASILOXANE; DIMETHICONE; BHT; SILICA; LINALOOL, (+/-)-; STEARYL ALCOHOL; GLYCINE; CALCIUM CHLORIDE; C12-15 ALKYL BENZOATE; PPG-14 BUTYL ETHER; STEARETH-100

Dove Men + Care Sandalwood + Amber 72H Antiperspirant

DESCRIPTION

Dove Men + Care Sandalwood + Amber 72H Antiperspirant

ACTIVE INGREDIENT

Aluminum Sesquichlorohydrate (12.8%)

PURPOSE

antiperspirant

INDICATIONS AND USAGE

reduces underarm wetness

WARNINGS

For external use only. Do not use on broken skin. Stop use if rash or irritation occurs. Ask a doctor before use if you have kidney disease.

Keep out of reach of children. If swallowed, get medical help or contact a Poison Control Center right away.

DOSAGE AND ADMINISTRATION

apply to underarms only

INACTIVE INGREDIENT

Stearyl Alcohol, C12 -15Alkyl Benzoate,Cyclopentasiloxane, Isopropyl Palmitate,PPG -14 Butyl Ether,Hydrogenated Castor Oil, Glycine, PEG -8,Calcium Chloride,Dimethicone,Fragrance (Parfum), Polyethylene,Silica,Helianthus Annuus (Sunflower) Seed Oil, Steareth -100, BHT, Coumarin, Hexyl Cinnamal, Limonene, Linalool

QUESTIONS

Call 1-800-761-3683